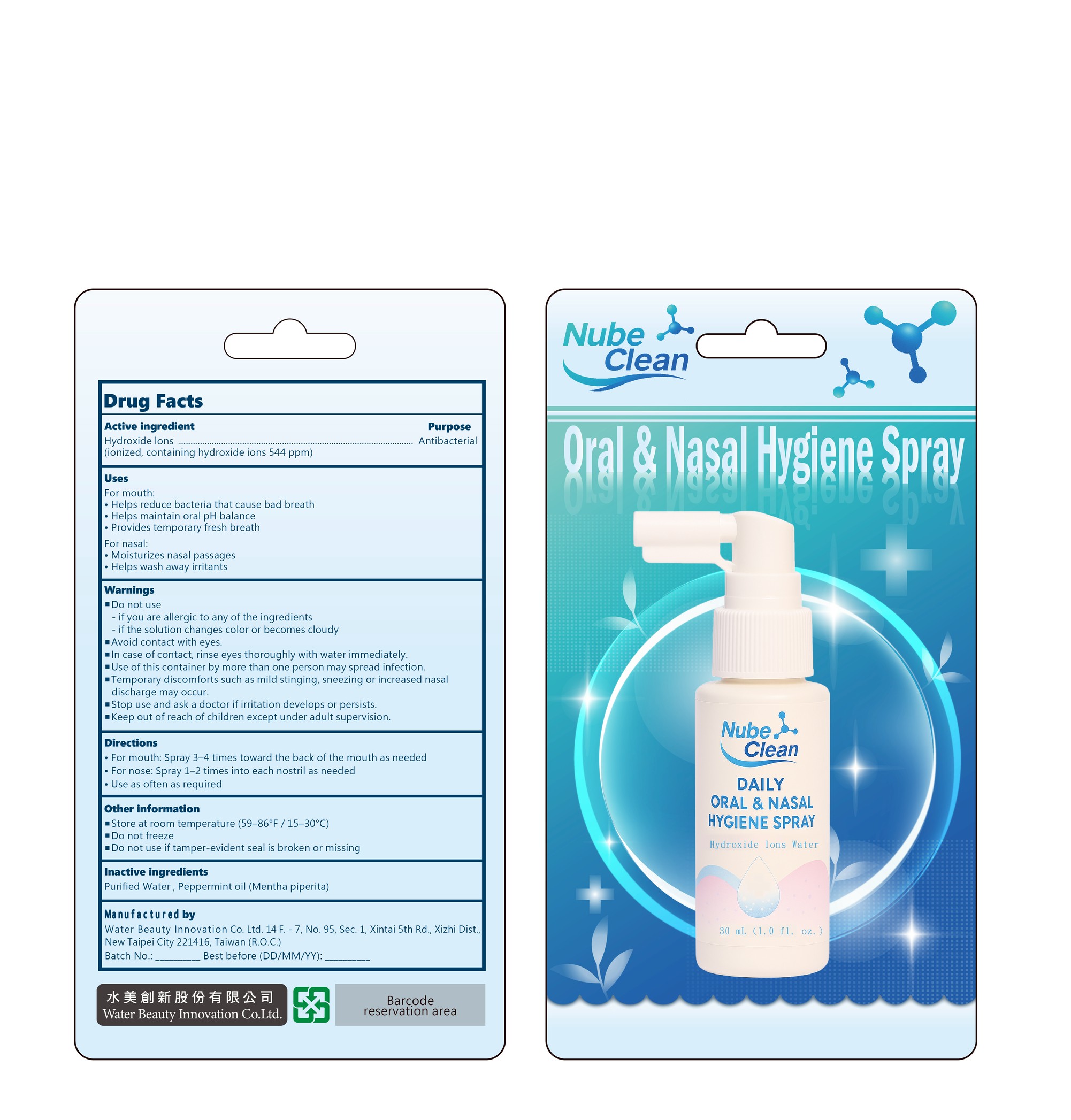 DRUG LABEL: ORAL and NASAL HYGIENE
NDC: 87406-002 | Form: LIQUID
Manufacturer: Water Beauty Innovation Co. Ltd.
Category: otc | Type: HUMAN OTC DRUG LABEL
Date: 20260212

ACTIVE INGREDIENTS: HYDROXIDE ION 0.2 g/100 mL
INACTIVE INGREDIENTS: WATER; PEPPERMINT OIL

Water Beauty 002-01

ACTIVE INGREDIENT

Hydroxide ions
(Ionized, containing hydroxide ions 544 ppm)

PURPOSE

Antibacterial

INDICATIONS AND USAGE

For mouth:
• Helps reduce bacteria that cause bad breath
• Helps maintain oral pH balance
• Provides temporary fresh breath

For nasal:
• Moisturizes nasal passages
• Helps wash away irritants

WARNINGS

• Avoid contact with eyes.
• In case of contact, rinse eyes thoroughly with water immediately.
• Use of this container by more than one person may spread infection.
• Temporary discomfort such as mild stinging, sneezing or increased nasal discharge may occur.

DO NOT USE

– if you are allergic to any of the ingredients
– if the solution changes color or becomes cloudy

• Stop use and ask a doctor if irritation develops or persists.

• Keep out of reach of children except under adult supervision.

DOSAGE AND ADMINISTRATION

• For mouth: Spray 3–4 times toward the back of the mouth as needed
• For nose: Spray 1–2 times into each nostril as needed
• Use as often as required

STORAGE AND HANDLING

• Store at room temperature (59–86°F / 15–30°C)
• Do not freeze
• Do not use if tamper-evident seal is broken or missing

INACTIVE INGREDIENT

Purified Water, Peppermint oil (Mentha piperita)